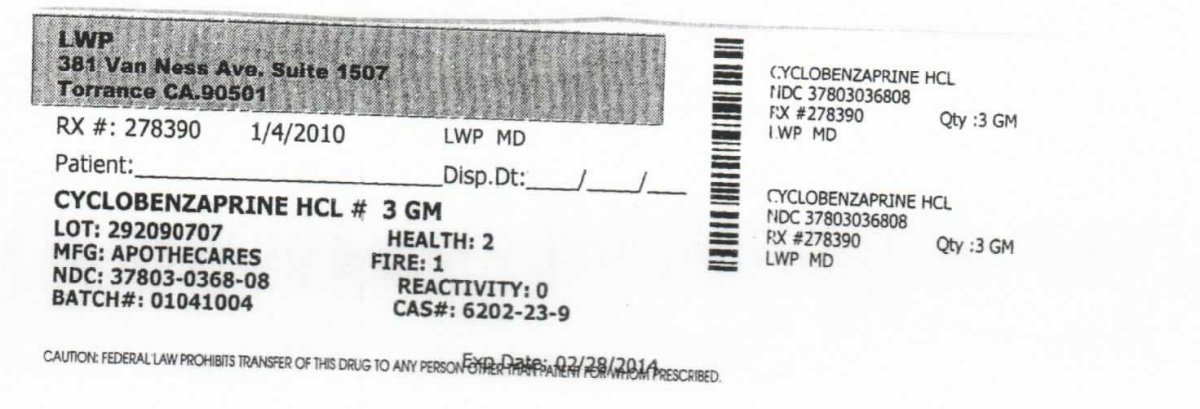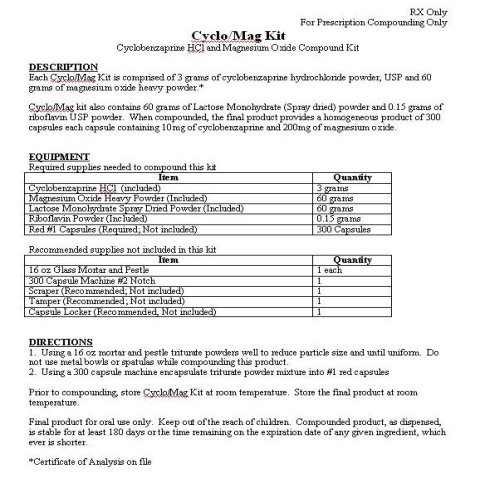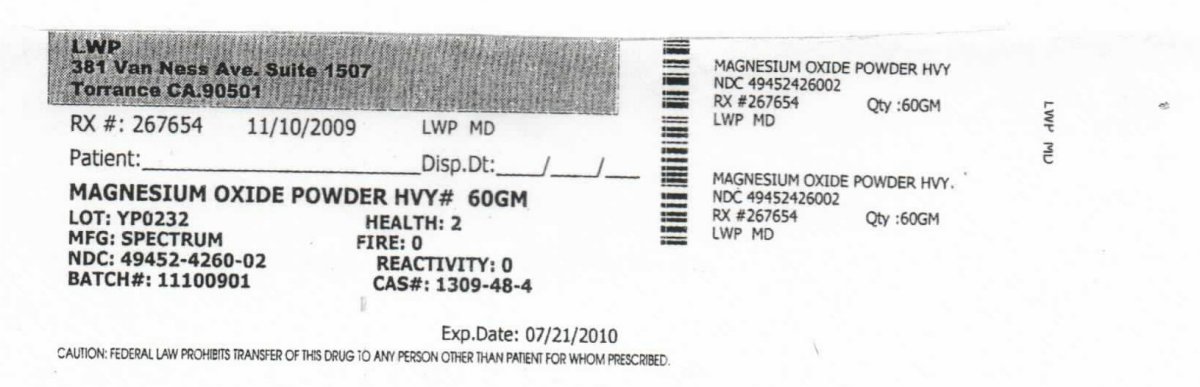 DRUG LABEL: Cyclo/Mag
NDC: 64038-313 | Form: KIT | Route: ORAL
Manufacturer: Living Well Pharmacy, Inc.
Category: prescription | Type: HUMAN PRESCRIPTION DRUG LABEL
Date: 20100305

ACTIVE INGREDIENTS: CYCLOBENZAPRINE HYDROCHLORIDE 1 g/1 g; MAGNESIUM OXIDE 1 g/1 g

CYCLO/MAG KIT

PACKAGE LABEL

RX #: 278390 1/4/2010 LWP MD

CYLCOBENZAPRINE HCL #3 GM

LOT: 292090707 HEALTH: 2

MFG: APOTHECARES FIRE:1

NDC: 37803-0368-08 REACTIVITY:0

BATCH #: 01041004 CAS:6202-23-9

PACKAGE LABEL

RX #: 267654 11/10/2009 LWP MD
MAGNESIUM OXIDE POWDER HVY #60 GM
LOT: YP0232 HEALTH: 2
MFG: SPECTRUM FIRE:0
NDC: 49452-4260-02 REACTIVITY:0
BATCH #: 11100901 CAS:1309-48-4

DESCRIPTION

1. RX Only

For Prescription Compounding Only

Cyclo/Mag Kit
Cyclobenzaprine HCl and Magnesium Oxide Compound Kit
Description
Each Cyclo/Mag Kit is comprised of 3 grams of cyclobenzaprine hydrochloride powder, USP and
60 grams of magnesium oxide heavy powder.
Certificate of Analysis on File
Cyclo/Mag Kit also contains 60 grams of Lactose Monohydrate (Spray dried) powder and 0.15 grams of
riboflavin USP powder. When compounded, the final product provides a homogeneous product of 300
capsules each capsule containing 10mg of cyclobenzaprine and 200mg of magnesium oxide.

INDICATIONS AND USAGE

Equipment

Required supplies needed to compound this kit

Equipment
Item | Quantity
Cyclobenzaprine HCl (Included) | 3 grams
Magnesium Oxide Heavy Powder (Included) | 60 grams
Lactose Monohydrate Spray Dried Powder (Included) | 60 grams
Riboflavin Powder (Included) | 0.15 grams
Red 1 Capsules (Required Not Included) | 300 Capsules

DRUG AND OR LABORATORY TEST INTERACTIONS

Equipment

Recommended supplies not included in this kit

Equipment
Item | Quantity
16 oz Glass Mortar and Pestle | 1 each
300 Capsule Machine Number 2 Notch | 1
Scraper (Recommended Not Included) | 1
Tamper (Recommended Not Included) | 1
Capsule Locker (Recommended Not Included) | 1

Directions

1. Using a 16 oz mortar and pestle triturate powders well to reduce particle size until uniform. Do not use metal bowls or spatulas while

compounding this product.

2. Using a 300 capsule machine encapsulate triturate powder mixture into number 1 red capsules

STORAGE AND HANDLING

Prior to compounding, store Cyclo/Mag Kit at room temperature. Store the final product at room temperature.

WARNINGS AND PRECAUTIONS

Final product for oral use only. Keep out the reach of children. Compounded product, as dispensed,

is stable for at least 180 days or the time remaining on the expiration date of any given ingredient,

which ever is shorter.